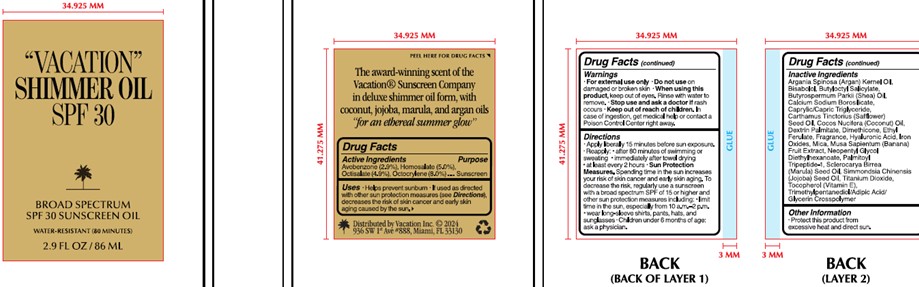 DRUG LABEL: Vacation Shimmer Oil
NDC: 80641-524 | Form: OIL
Manufacturer: Vacation Inc
Category: otc | Type: HUMAN OTC DRUG LABEL
Date: 20240516

ACTIVE INGREDIENTS: AVOBENZONE 2.9 g/100 mL; HOMOSALATE 5 g/100 mL; OCTOCRYLENE 8 g/100 mL; OCTISALATE 4.9 g/100 mL
INACTIVE INGREDIENTS: ETHYL FERULATE; DEXTRIN PALMITATE (CORN; 20000 MW); DIMETHICONE; TITANIUM DIOXIDE; TOCOPHEROL; ARGANIA SPINOSA SEED; BUTYLOCTYL SALICYLATE; TRIMETHYLPENTANEDIOL/ADIPIC ACID/GLYCERIN CROSSPOLYMER (25000 MPA.S); CALCIUM SODIUM PHOSPHATE; SCLEROCARYA BIRREA SEED OIL; SHEANUT OIL; MEDIUM-CHAIN TRIGLYCERIDES; COCONUT OIL; FERRIC OXIDE RED; MICA; SAFFLOWER OIL; HYALURONIC ACID; PALMITOYL TRIPEPTIDE-1; JOJOBA OIL; LEVOMENOL; NEOPENTYL GLYCOL DIETHYLHEXANOATE; BANANA

Vacation Shimmer Oil SPF 30

Inactives

Argania Spinosa Kernel Oil

Bisabolol

Butyloctyl Salicylate

Butyrospermum Parkii (Shea) Oil

Calcium Sodium Borosilicate

Caprylic/Capric Triglyceride

Carthamus Tinctorius (Safflower) Seed Oil

Cocos Nucifera (Coconut) Oil

Dextrin Palmitate

Dimethicone

Ethyl Ferulate

Fragrance*

Hyaluronic Acid

Iron Oxides

Mica

Musa Sapientum (Banana) Fruit Extract

Neopentyl Glycol Diethylhexanoate

Palmitoyl Tripeptide-1

Sclerocarya Birrea Seed Oil

Simmondsia Chinensis (Jojoba) Seed Oil

Titanium Dioxide

Tocopherol

Trimethylpentanediol/Adipic Acid/Glycerin Crosspolymer

Purpose

Sunscreen

Indications and Usage

Helps prevent sunburn

If used as directed with other sun protection measures (see Directions), decreases the risk of skin cancer and early skin aging caused by the sun

Warnings

For external use only

Do not used on damaged or broken skin

When using this product keep out of eyes. Rinse with water to remove.

Stop use and ask doctor if rash occurs

Keep out of reach of children

In case of ingestion, get medical help or contact a Poison Control Center right away

Dosage and Administration

Apply liberally for 15 minutes before sun exposure

Reapply after 80 minutes of swimming or sweating

Immediately after towel drying

At least every 2 hours